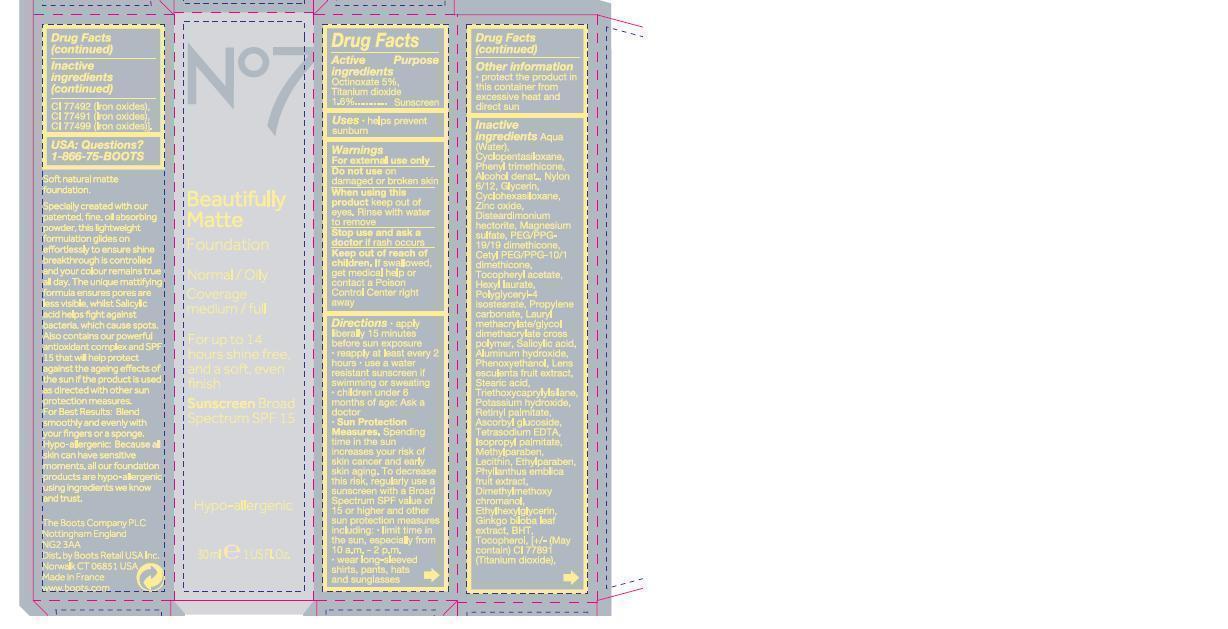 DRUG LABEL: No7 Beautifully Matte Foundation Sunscreen Broad Spectrum SPF 15 Mocha
NDC: 61589-6502 | Form: EMULSION
Manufacturer: BCM Cosmetique SAS
Category: otc | Type: HUMAN OTC DRUG LABEL
Date: 20121106

ACTIVE INGREDIENTS: OCTINOXATE 1.5 g/30 g; TITANIUM DIOXIDE 0.48 g/30 g
INACTIVE INGREDIENTS: WATER; CYCLOMETHICONE 5; GLYCERIN; NYLON-12; LECITHIN, SOYBEAN; ZINC OXIDE; CYCLOMETHICONE 6; MAGNESIUM SULFATE; ASCORBYL GLUCOSIDE; PHENOXYETHANOL; BUTYLENE GLYCOL; PEG/PPG-19/19 DIMETHICONE; .ALPHA.-TOCOPHEROL, DL-; PHENYL TRIMETHICONE; PROPYLENE CARBONATE; LAURYL METHACRYLATE/GLYCOL DIMETHACRYLATE CROSSPOLYMER; CETYL PEG/PPG-10/1 DIMETHICONE (HLB 1.5); HEXYL LAURATE; POLYGLYCERYL-4 ISOSTEARATE; METHYLPARABEN; SALICYLIC ACID; ETHYLPARABEN; POTASSIUM HYDROXIDE; VITAMIN A PALMITATE; TRIETHOXYCAPRYLYLSILANE; ALUMINUM HYDROXIDE; ALCOHOL; STEARIC ACID; ETIDRONATE TETRASODIUM; BUTYLATED HYDROXYTOLUENE; ETHYLHEXYLGLYCERIN; ISOPROPYL PALMITATE; TOCOPHEROL; PHYLLANTHUS EMBLICA FRUIT; GINKGO BILOBA LEAF OIL; TITANIUM DIOXIDE

No7 Beautifully Matte Foundation Mocha

Warnings

For external use only

Do not use on damaged or broken skin

When using this product keep out of eyes. Rinse with water to remove

Stop use and ask a doctor if rash occurs

Keep out of reach of children. If swallowed get medical help or contact a Poison control centre right away

Drug Facts

active ingredients octinoxate 5%

Titanium Dioxide 1.6%

purpose sunscreen

Uses

helps prevent sunburn

if used as directed with other sun protection measures (see directions) decreases the risk of skin cancer and early skin aging caused by the sun

Directions

apply liberally 15 minutes before sun exposure

reapply at least every 2 hours

use a water resistant sunscreen if swimming or sweating

children under 6 months of age ask a doctor

sun protectin measures

spending time in the sun increases your risk of skin cancer and early skin aging. to decrease this risk, regularly use a sunscreen with a broad spectrum SPF value of 15 or higher and other sun protection measures including limit time in the sun especially from 10 am to 2 pm, wear long sleeved shirts, pants, hats and sunglasses

STORAGE AND HANDLING

protect the product in this container from excessive heat and direct sun

DESCRIPTION

Soft natural matte foundation

Specially created with our patented, fine, oil absorbing powder, this lightweight formulation glides on effortlessly to ensure shine breakthrough is controlled and your colour remains true all day. The unique mattifying formula ensures pores are less visble, whilst Salicylic acid helps fight against bacteria, which cause spots. Also contains our powerful anitoxidant complex and SPF 15 that will help protect against the ageing effects of the sun if the product is used as directed with other sun protection measures. For best results blend smoothly and evenly with your fingers or a sponge. Hypo-allergenic because all skin can have sensitive moments, all our foundation products are hypo-allergenic using ingredients we know and trust.

inactive ingredients

aqua (water), cyclopentasiloxane, phenyl trimethicone, alcohol denat, nylon 6/12, glycerin, cyclohexsiloxane, zinc oxide, disteardimonium hectorite, magnesium sulfate, PEG PPG 19/19 dimethicone, tocopheryl acetate, hexyl laurate, polyglyceryl-4- isostearate, propylene carbonate,lauryl methacrylate/glycol dimethacrylate cross polymer, salicylic acid, aluminum hydroxide, phenoxyethanol, lens esculenta fruit extract, stearic acid, triethoxycaprylylsilane, potassium hydroxide, retinyl palmitate, ascorbyl glucoside, tetrasodium edta, isopropyl palmitate, methylparaben, lecithin, ethylparaben, phyllanthus emblica fruit extract, dimethoxyl chromanol, ethylhexylglycerin, ginkgo biloba leaf extract, BHT, tocopherol, may contain CI 77891 (titanium dioxide).

PATIENT COUNSELING INFORMATION

USA Questions?

1-866-75-BOOTS

The Boots Company PLC

Nottingham England NG2 3AA

Dist by Boots Retail USA Inc

Norwalk CT 06851 USA

Made in France

www.Boots.Com